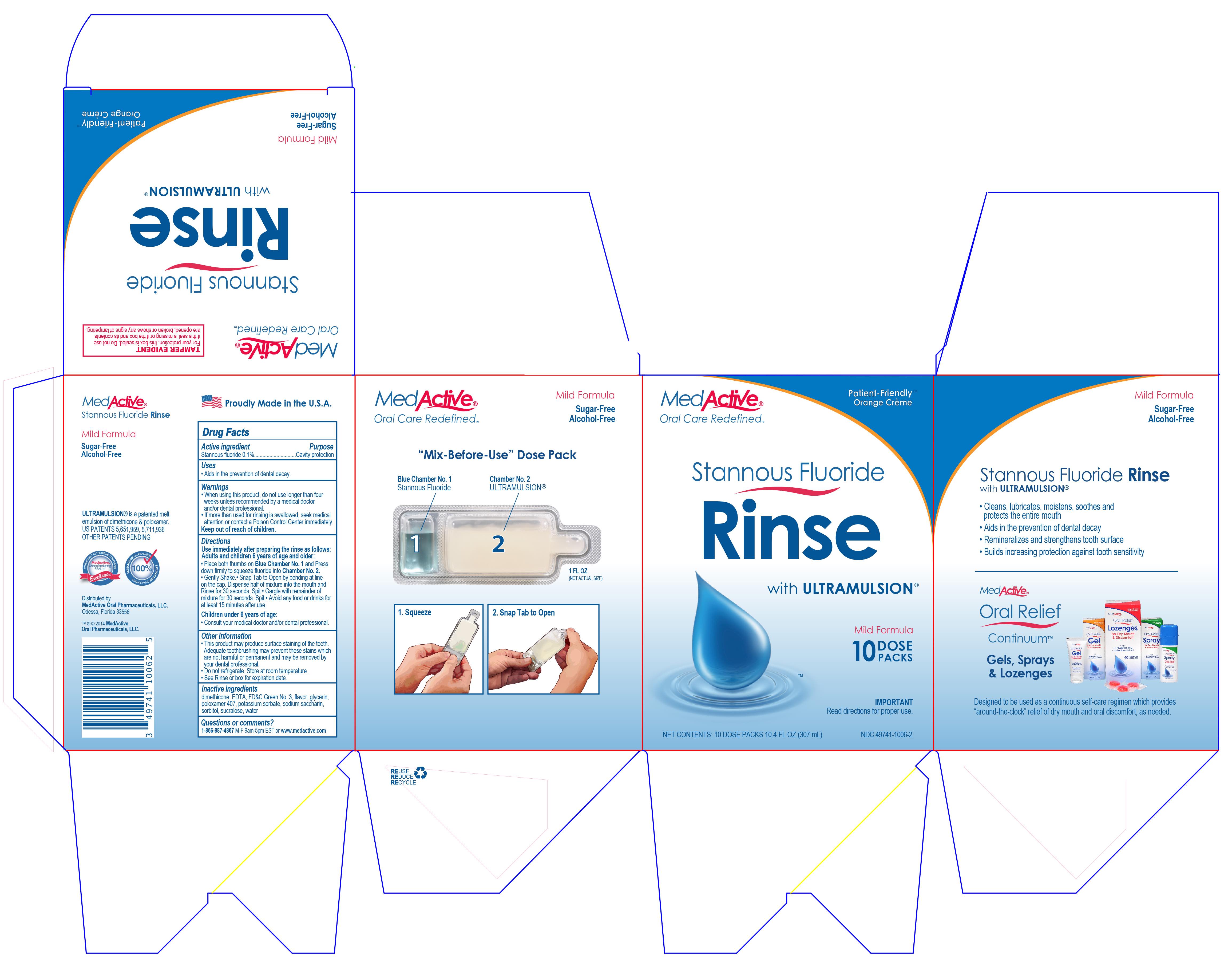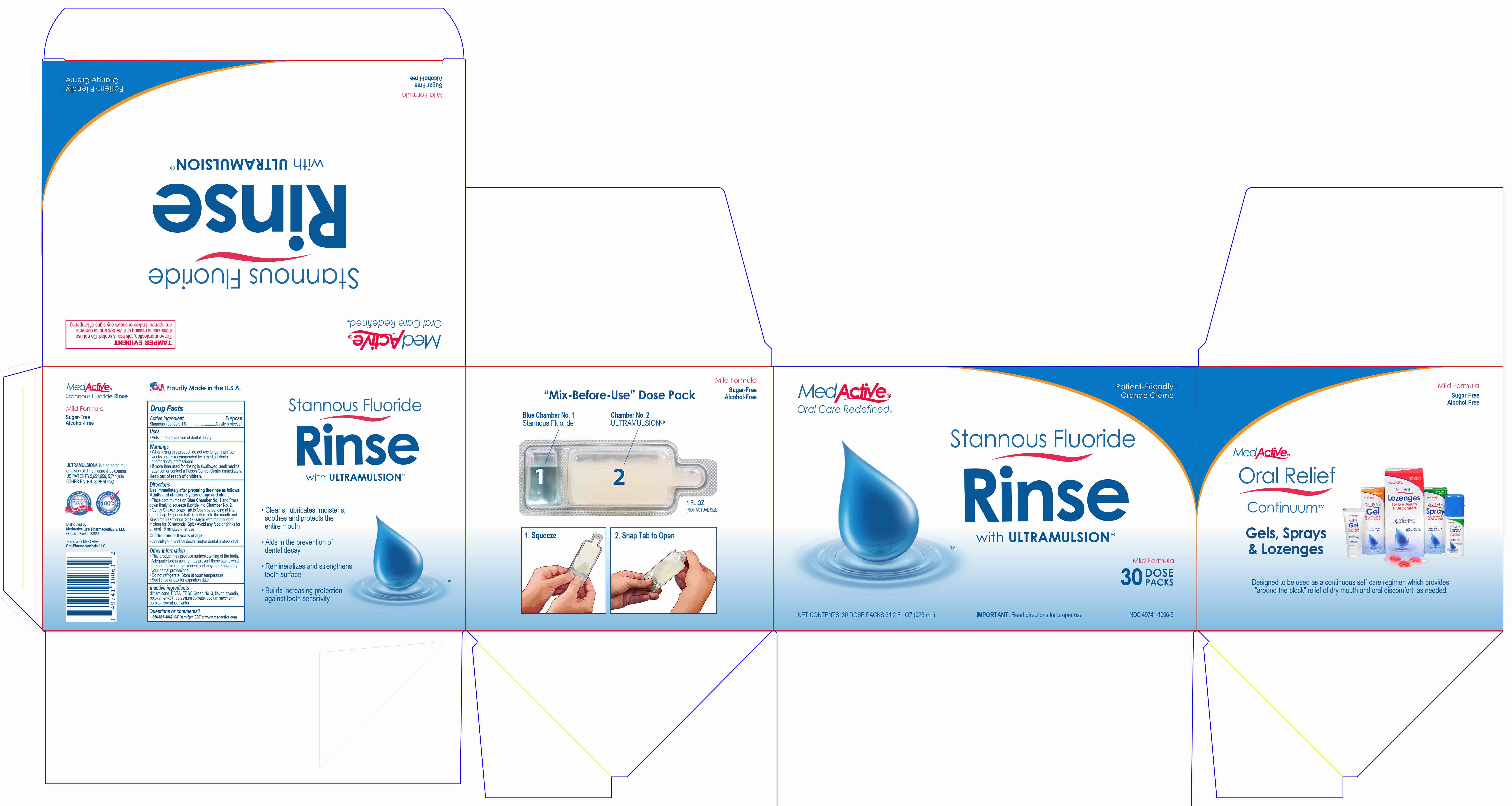 DRUG LABEL: MedActive Patient Friendly Stannous Fluoride Rinse
NDC: 49741-1006 | Form: KIT | Route: ORAL
Manufacturer: Integrate Oral Care, LLC.
Category: otc | Type: HUMAN OTC DRUG LABEL
Date: 20211230

ACTIVE INGREDIENTS: STANNOUS FLUORIDE 6.3 mg/1 mL
INACTIVE INGREDIENTS: GLYCERIN 1 mL/1 mL; FD&C GREEN NO. 3 1 mL/1 mL; DIMETHICONE; EDETIC ACID; POLOXAMER 407; SACCHARIN SODIUM; SORBITOL; SUCRALOSE; WATER; POTASSIUM SORBATE

Active Ingredient

Stannous Fluoride 0.1%

Uses

Aids in the prevention of dental decay.

Warnings

- When using this product, do not use longer than four weeks unless recommended by a medical doctor and/or dental professional.
- If more than used for rinsing is swallowed, seek medical attention or contact a Poison Control Center immediately.

Directions

Use immediately after preparing the rinse as follows:

Adults and children 6 years or age and older:

- Place both thumbs on Blue Chamber No. 1 and Press down firmly to squeeze fluoride into Chamber No. 2.
- Gently Shake.
- Snap Tab to Open by bending at line on the cap. Dispense half of mixture into the mouth and Rinse for 30 seconds. Spit.
- Gargle with remainder of mixture for 30 seconds. Spit.
- Avoid any food or drinks for at least 15 minutes after use.

Children under 6 years of age:

- Consult your medical doctor and/or dental professional.

Other Information

- This product may produce surface staining of the teeth. Adequate toothbrushing may prevent these stains which are not harmful or permanent and may be removed by your dental professional.
- Do not refrigerate. Store at room temperature.
- See Rinse or box for expiration date.

Inactive Ingredients

dimethocone, EDTA, FD&C Green No. 3, flavor, glycerin, poloxamer 407, potassium sorbate, sodium saccharin, sorbital, sucralose, water

Questions or comments?

1-866-887-4867 M-F 9 am - 5 pm EST or www.integrateoralcare.com

Keep out of reach of children.

Purpose

Cavity Protection

Prinicpal Display Panel - 30 Dose Packs

MedActive

Oral Care Redefined

Patient-Friendly

Orange Crème

Stannous Fluoride Rinse with ULTRAMULSION

Mild Formula

30 Dose Packs

NET CONTENTS: 30 DOSE PACKS 31.2 FL OZ (923 mL)

IMPORTANT: Read directions for proper use.

NDC 49741-1005-3

Principal Display Panel - 10 Dose Packs

MedActive

Oral Care Redefined

Patient-Friendly

Orange Crème

Stannous Fluoride Rinse with ULTRAMULSION

Mild Formula

10 Dose Packs

NET CONTENTS: 10 DOSE PACKS 10.4 FL OZ (307 mL)

IMPORTANT: Read directions for proper use.

NDC 49741-1006-2